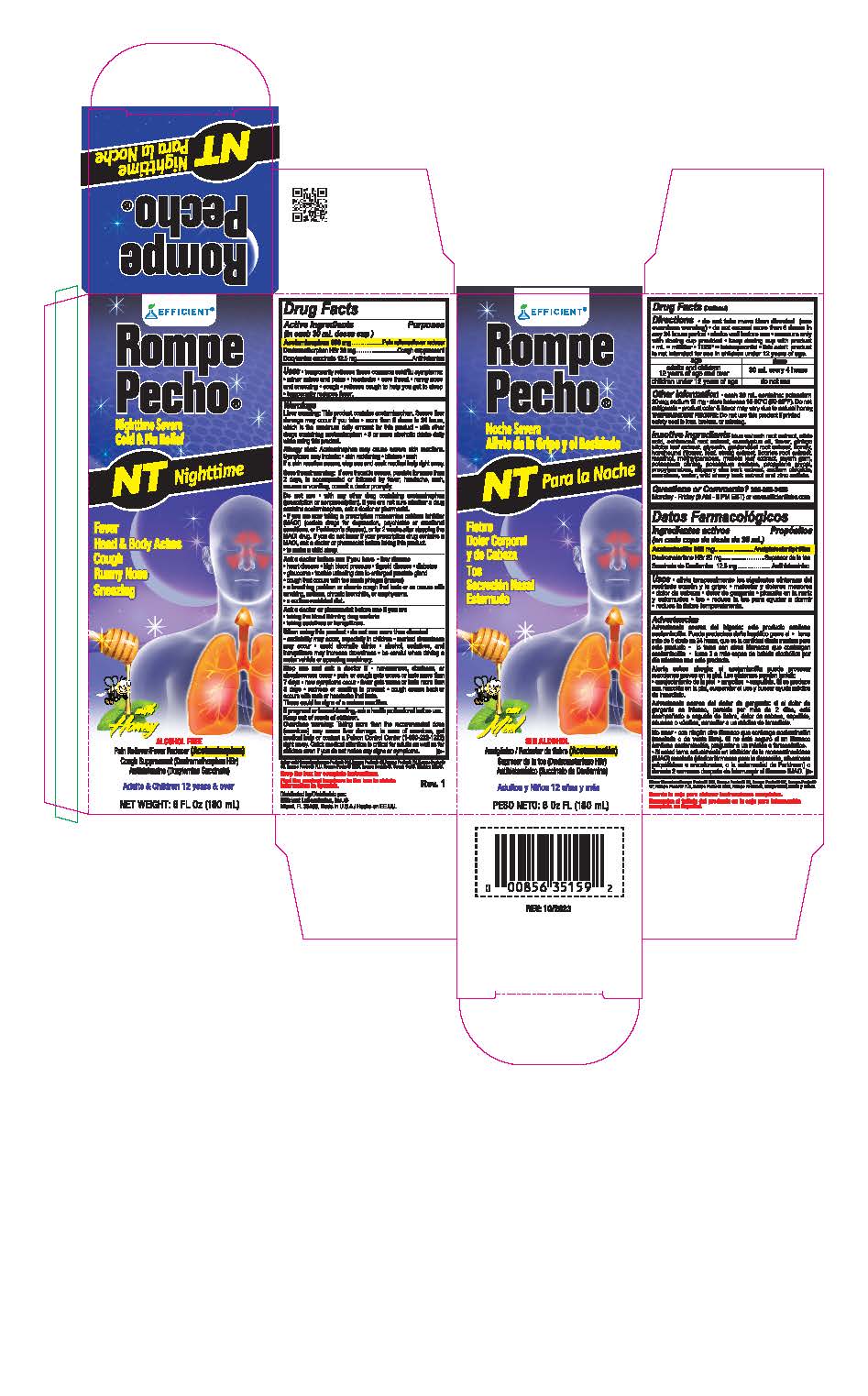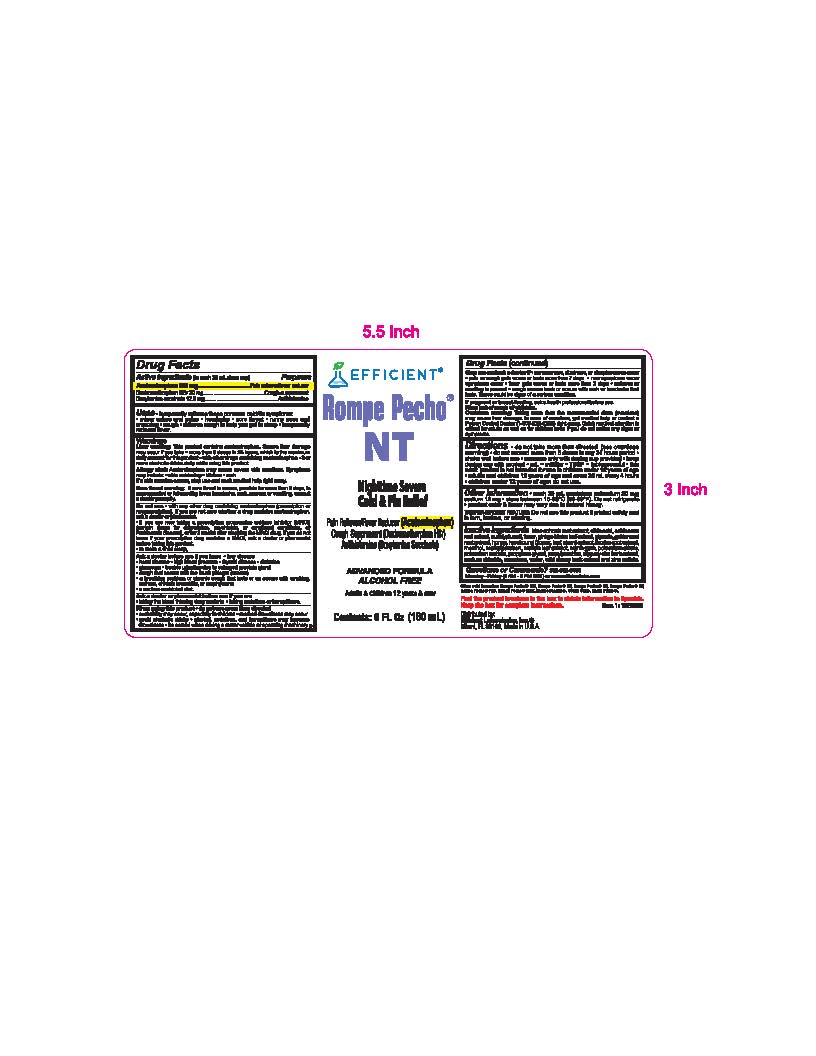 DRUG LABEL: Rompe Pecho NT
NDC: 58593-003 | Form: LIQUID
Manufacturer: Efficient Laboratories Inc
Category: otc | Type: HUMAN OTC DRUG LABEL
Date: 20241008

ACTIVE INGREDIENTS: ACETAMINOPHEN 650 mg/30 mL; DEXTROMETHORPHAN HYDROBROMIDE 20 mg/30 mL; DOXYLAMINE SUCCINATE 12.5 mg/30 mL
INACTIVE INGREDIENTS: POTASSIUM CITRATE ANHYDROUS; CAULOPHYLLUM THALICTROIDES ROOT; GLYCERIN; ECHINACEA ANGUSTIFOLIA ROOT; EUCALYPTUS OIL; GINKGO BILOBA LEAF OIL; GOLDENSEAL; HONEY; ANHYDROUS CITRIC ACID; HOREHOUND; MENTHOL; METHYLPARABEN; LICORICE; MULLEIN LEAF; POTASSIUM SORBATE; PROPYLENE GLYCOL; PROPYLPARABEN; WATER; ULMUS RUBRA BARK; SODIUM CHLORIDE; PRUNUS SEROTINA BARK; ZINC SULFATE; MYRRH; SUCRALOSE

Rompe Pecho NT

Active Ingredients:(in each 30ml doses cup) Purpose

Acetaminophen 650mg ............................................................ Pain reliever/fever reducer

Dextromethorphan HBr 20 mg ..................................................Cough Suppressant

Doxylamine succinate 12.5 mg ................................................ Antihistamine

Purpose

Pain reliever/fever reducer

Cough Suppressant

Antihistamine

Warnings

Liver warning: This product contains acetaminophen. Severe liver damage may occur f you take • more than 6 doses in 24 hours, which is the maximum daily amount for this prcx:luct • with other drugs containing acetaminophen • 3 or more alcoholic drinks daily wh le using this product.

Allergy alert: Acetaminophen may cause severe skin reactions. Symptoms may include: • skin reddening • blisters• rash
If a skin reaction occurs,stop use and seek medical help right away.

Sore throat warning: If sore throat is severe,persists for more than 2 days, is accompanied or followed by fever, headache, rash, nausea or vomiting,consult a doctor promptly.

Do not use • with any other drug containing acetaminophen (prescription or nonprescription). If you are not sure whether a drug contains acetaminophen,ask a doctor or phannacist.
• if you are now taking a prescription monoamine oxidase inhibitor (MAOI) (certain drugs for depression, psychiatric or emotional conditions,or Parkinson'sdisease),or for 2 weeks after stopping the MAOI drug. If you do not know if your prescription drug contains a MAOI,ask a doctor or pharmacist before taking this product.
• to make a childsleep_

PREGNANCY OR BREAST FEEDING

If pregnant or breast-feeding,ask a health professional before use.

Keep out of reach of children.

Overdose warning: Taking more than the recommended dose (overdose) may cause liver damage. In case of overdose, get medical help or contact a Poison Control Center (1-800-222-1222) right away. Quick medical attention is critical for adults as well
as for children even if you do not notice any signs or symptoms.

DOSAGE AND ADMINISTRATION

Directions do not take more than directed (see overdose warning)

- Do not exceed more than 6 doses in any 24-hour period
- Shake well before use
- measure only with dosing cup provided
- keep dosing cup with product
- mL=miliiter TSP=teaspoonful
- this adult product is not intended for use in children under 12 years of age

Age | - Dose
- adults and children 12 years of age and over | - 30 mL every 4 hours
- children under 12 years of age | - do not use

Uses

• temporarily relieves these common cold/flu symptoms:
• minor aches and pains• headache• sore throat• runny nose and sneezing • cough • relieves cough to help you get to sleep
• temporarily reduces fever.

INACTIVE INGREDIENT

Inactive ingredients: blue cohosh root extract, citric acid, echinacea root extract, eucalyptus oil, flavor, ginkgo biloba leaf extract, glycerin, goldenseal root extract, honey, horehound (flower, leaf, stem) extract, licorice root extract, menthol, methylparaben, mullein leaf extract, myrrh gum, potassium citrate, potassium sorbate, propylene glycol, Propylparaben, slippery elm bark extract, sodium chloride, sucralose, water, wild cherry bark extract and zinc sulfate.

Questions or Comments?

305-805-3456 Monday - Friday 9AM to 5PM EST

www.efficientlabs.com

Distributed by

Efficient Laboratories, Inc., Miami, Fl 33166

Made in U.S.A.

Ask a doctor or pharmacist before use if you are:

• taking the blood thinning drug warfarin
• taking sedatives or tranquilizers.

When using this product • do not use more than directed
• excitability may occur, especially in children• marked drowsiness may occur • avoid alcoholic
drinks • alcohol, sedatives, and tranquilizers may increase drowsiness • be careful when driving a
motor vehicle or operating machinery.

Ask a doctor before use if you have:

• liver disease • heart disease • high blood pressure • thyroid disease • diabetes • glaucoma • trouble urinating due to enlarged prostate gland • cough that occurs with too much phlegm (mucus) • a breathing problem or chronic cough that lasts or as occurs with smoking, asthma, chronic bronchitis,or emphysema • a sodium-restricted diet.

Stop use and ask a doctor if • nervousness, dizziness, or
sleeplessness occur • pain or cough gets worse or lasts more than 7 days • new symptoms occur •fever gets worse or lasts more than 3 days • redness or swelling is present • cough comes back or occurs with rash or headache that lasts.
These could be signs of a serious condition.